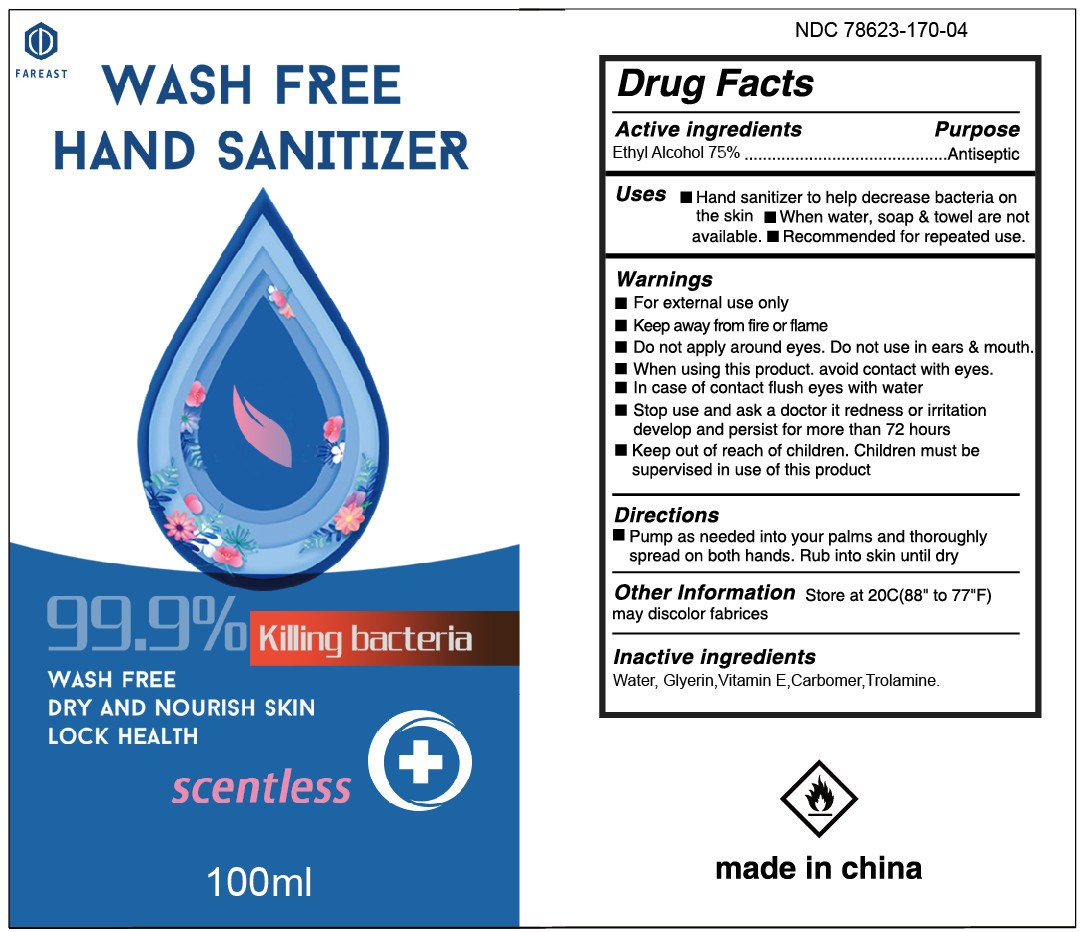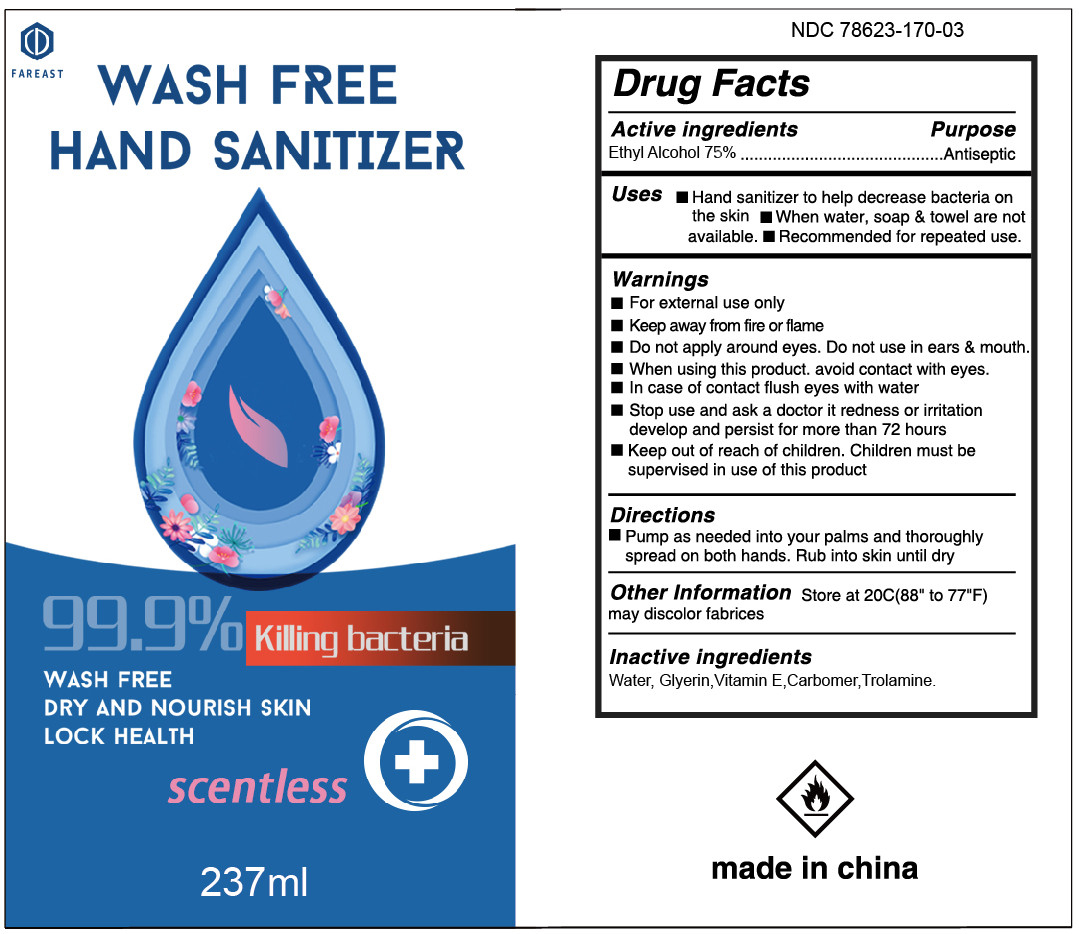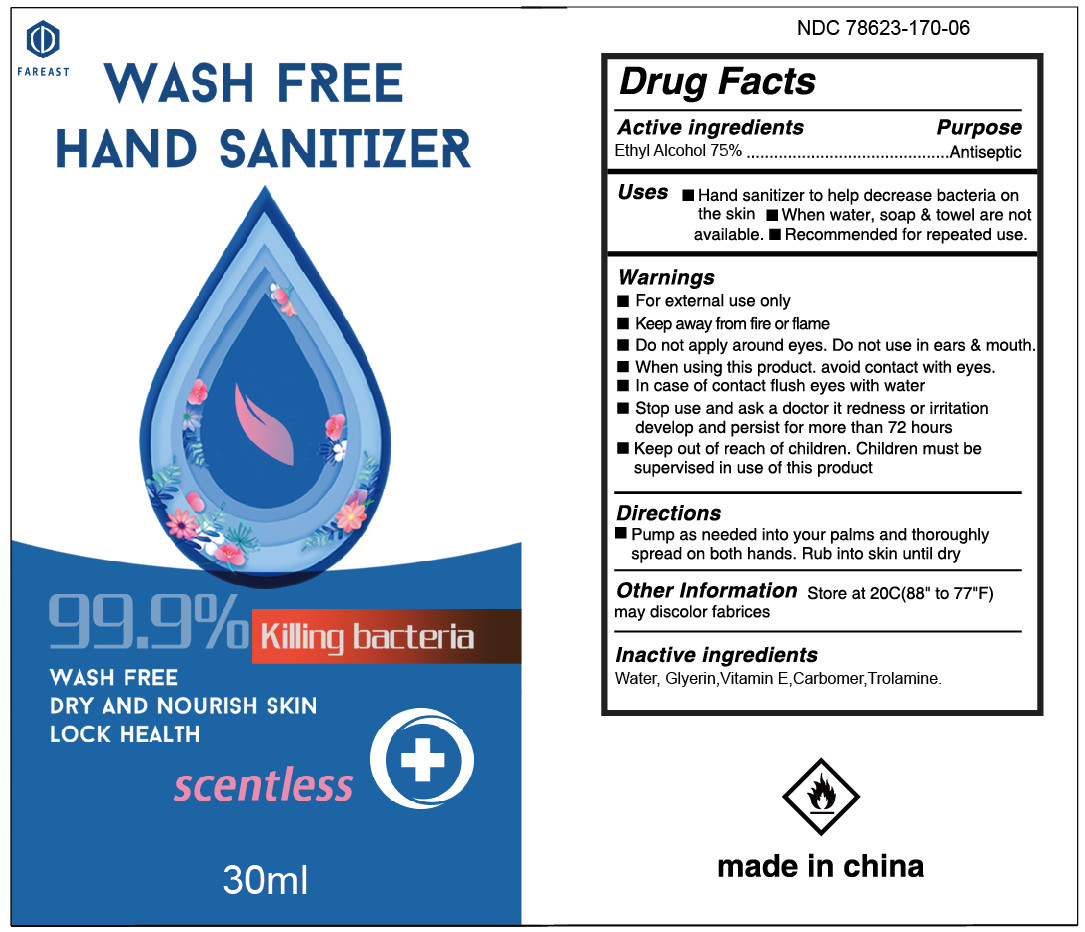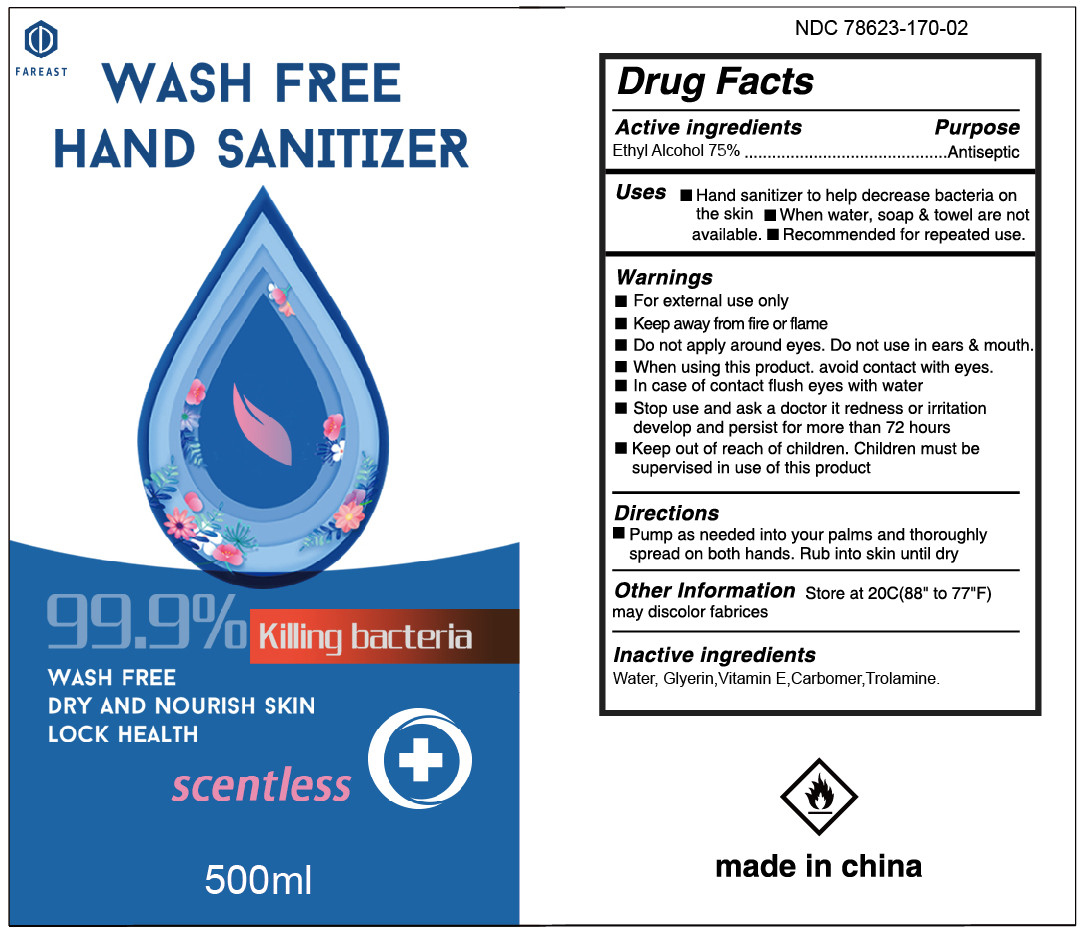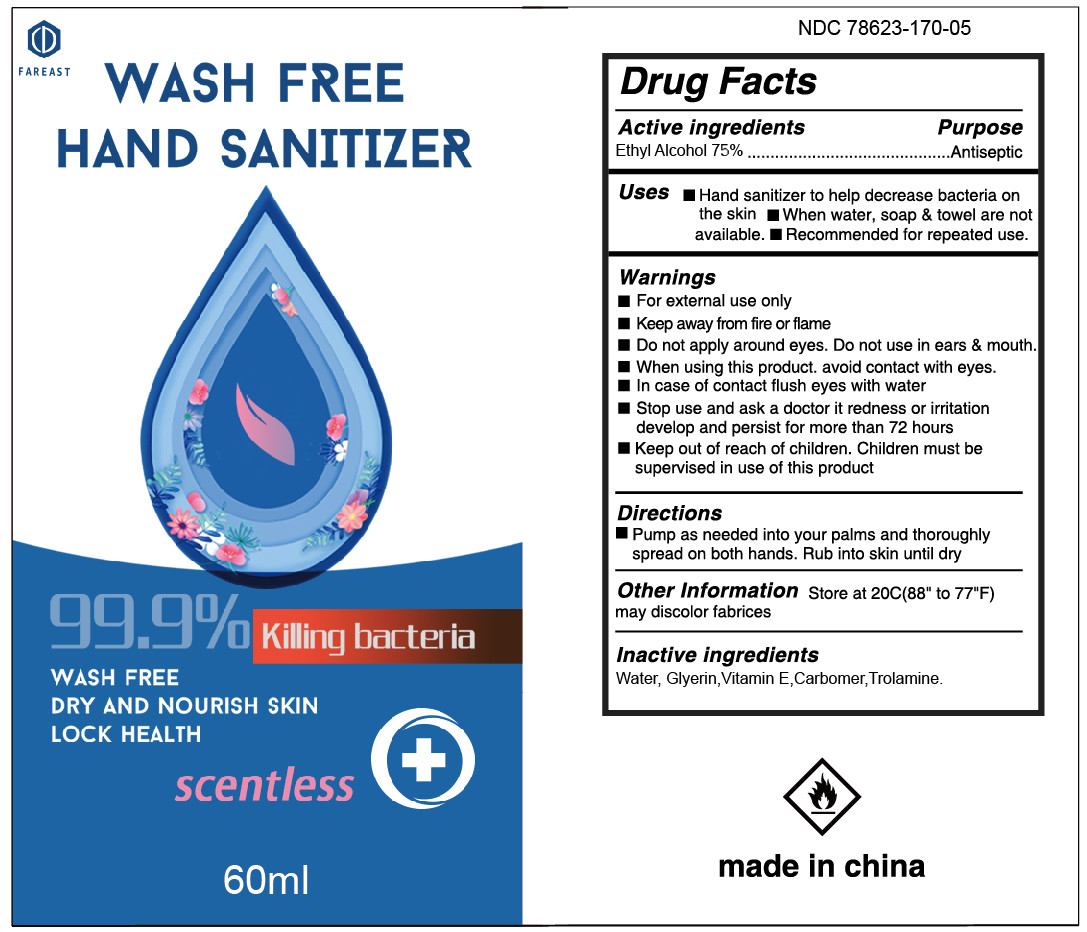 DRUG LABEL: Hand Sanitizer
NDC: 78623-475 | Form: GEL
Manufacturer: ningbo fareast industry co.,ltd
Category: otc | Type: HUMAN OTC DRUG LABEL
Date: 20210104

ACTIVE INGREDIENTS: ALCOHOL 75 mL/100 mL
INACTIVE INGREDIENTS: WATER; CARBOMER HOMOPOLYMER, UNSPECIFIED TYPE; GLYCERIN; ALPHA-TOCOPHEROL; TROLAMINE

ACTIVE INGREDIENT

75%alcohol V/V purpose :antibacterial

INDICATIONS AND USAGE

to help reduce bacteria that potentially can cause disease.for use when soap and water are not available

WARNINGS

for external use only,flammable,keep away from heat or flame

DO NOT USE

in children less than 2 months of age
.on open skin wounds

when using this product keep out of eyes,ears,and mouth in case of contact with eyes,rinse eyes thorough with water
stop use and ask a doctor if irritation or rash occurs,these may be signs of a serious condition.
keep out of reach of children,if swallowed,get medical help or contact a poison control center right away.

stop use and ask a doctor if irriation or rash occurs,these may be signs of a serious condition

keep out of reach of children ,if swallowed, get medical help or contact a posion control center right away .

DOSAGE AND ADMINISTRATION

place enough product on hands to cover all surface,rub hands together until dry
supervise children under 6 years when using this product to avoid swallowing

PACKAGE LABEL

500ml NDC: 78623-475-02

237ml NDC: 78623-475-03

100ml NDC: 78623-475-04

60ml NDC: 78623-475-05

30ml NDC: 78623-475-06